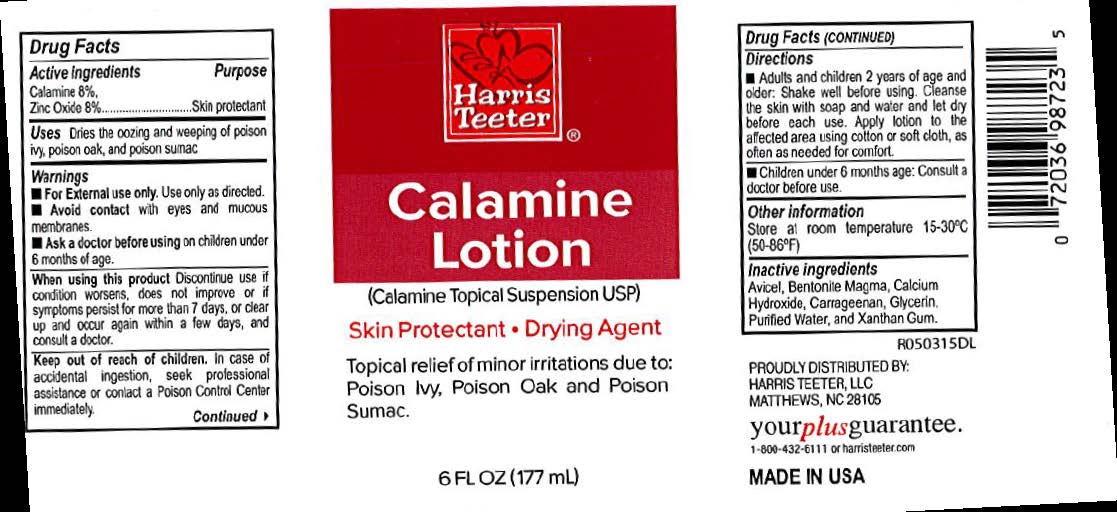 DRUG LABEL: Harris Teeter Calamine
NDC: 69256-413 | Form: LIQUID
Manufacturer: Harris Teeter, LLC.
Category: otc | Type: HUMAN OTC DRUG LABEL
Date: 20231220

ACTIVE INGREDIENTS: ZINC OXIDE 160 mg/1 mL
INACTIVE INGREDIENTS: CELLULOSE, MICROCRYSTALLINE; BENTONITE; CALCIUM HYDROXIDE; CARRAGEENAN; GLYCERIN; WATER; XANTHAN GUM

Harris Teeter Calamine Lotion

Harris Teeter Calamine Lotion

Drug Facts

Active Ingredient

Calamine 8%

Active Ingredient

Zinc Oxide 8%

Purpose

Skin Protectant

Uses

Dries the oozing and weeping of poison ivy, poison oak, and poison sumac.

Warnings

For external use only. Use only as directed.

Avoid contact with eyes and mucous membranes.

When using this product.

Discontinue use if condition worsens, does not improve or if symptoms persist for more than 7 days, or clear up and occur again within a few days and consult a doctor.

Keep out of reach of children.

In case of accidental ingestion, seek professional assistance or contact a Poison Control Center immediately.

Directions

- Adults and children 2 yrs. of age and older. Shake well before using. Cleanse the skin with soap and water and let dry before each use. Apply lotion to the affected area using cotton or soft cloth, as often as needed.
- Children under 6 months of age: Consult a doctor before use.

Other Information

store at room temperature 15o – 30oC (59o – 85oF)

Inactive Ingredients

Avicel, Bentonite Magma, Calcium Hydroxide, Carrageenan, Glycerin, Purified Water, and Xanthan Gum.